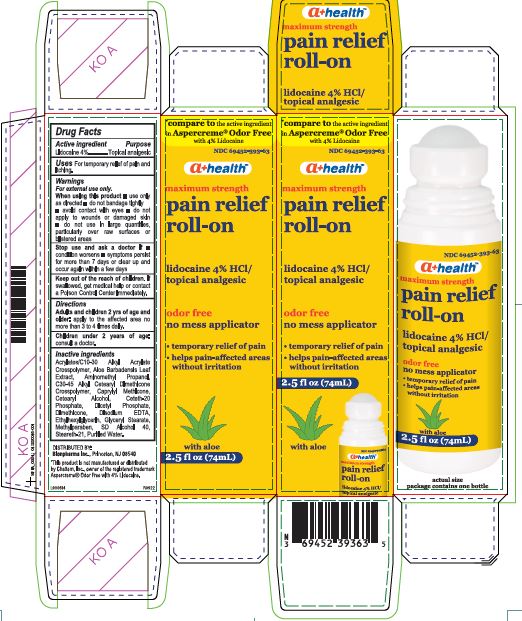 DRUG LABEL: pain relief roll-on
NDC: 69452-393 | Form: LIQUID
Manufacturer: Bionpharma Inc.
Category: otc | Type: HUMAN OTC DRUG LABEL
Date: 20241223

ACTIVE INGREDIENTS: LIDOCAINE HYDROCHLORIDE 4 g/100 mL
INACTIVE INGREDIENTS: AMINOMETHYLPROPANOL; WATER; STEARETH-21; ALCOHOL; METHYLPARABEN; CAPRYLYL TRISILOXANE; CARBOMER INTERPOLYMER TYPE A (55000 CPS); ALOE VERA LEAF; GLYCERYL MONOSTEARATE; ETHYLHEXYLGLYCERIN; EDETATE DISODIUM ANHYDROUS; DIHEXADECYL PHOSPHATE; CETETH-20 PHOSPHATE; DIMETHICONE; CETOSTEARYL ALCOHOL; HYDROXYETHYL ACRYLATE/SODIUM ACRYLOYLDIMETHYL TAURATE COPOLYMER (45000 MPA.S AT 1%)

pain relief roll-on

Active ingredient

Lidocaine 4%

Purpose

Topical analgesic

Uses

For temporarily relief of pain and itching.

Warnings

For external use only.

When using this product

- use only as directed
- do not bandage tightly
- avoid contact with eyes
- do not apply to wounds or damaged skin
- do not use in large quantities, particularly over raw surfaces or blistered areas

Stop use and ask a doctor

If

- condition worsens
- symptoms persist for more than 7 days or clear up and occur again within a few days

Keep out of reach of children.

If swallowed, get medical help or contact a Poison Control Center immediately.

Directions

Adults and children 2 years of age and older: apply to the affected area no more than 3 to 4 times daily.

Children under 2 years of age: consult a doctor.

Inactive ingredients

Acrylates/C10-30 Alkyl Acrylate Crosspolymer, Aloe Barbadensis Leaf Extract, Aminomethyl Propanol, C30-45 Alkyl Cetearyl Dimethicone Crosspolymer, Caprylyl Methicone, Cetearyl Alcohol, Ceteth-20 Phosphate, Dicetyl Phosphate, Dimethicone, Disodium EDTA, Ethylhexylglycerin, Glyceryl Stearate, Methylparaben, polysorbate 60, SD Alcohol 40, Steareth-21, Purified Water

Carton Label

*compare to the active ingredient

in Aspercreme® Odor Free

with 4 % Lidocaine

NDC 69452-393-63

a+health™

maximum strength

pain relief

roll-on

lidocaine 4% HCl/

topical analgesic

odor free

no mess applicator

- temporarary relief of pain
- helps pain-affected areas

without irritation

2.5 fl oz (74mL)

with aloe